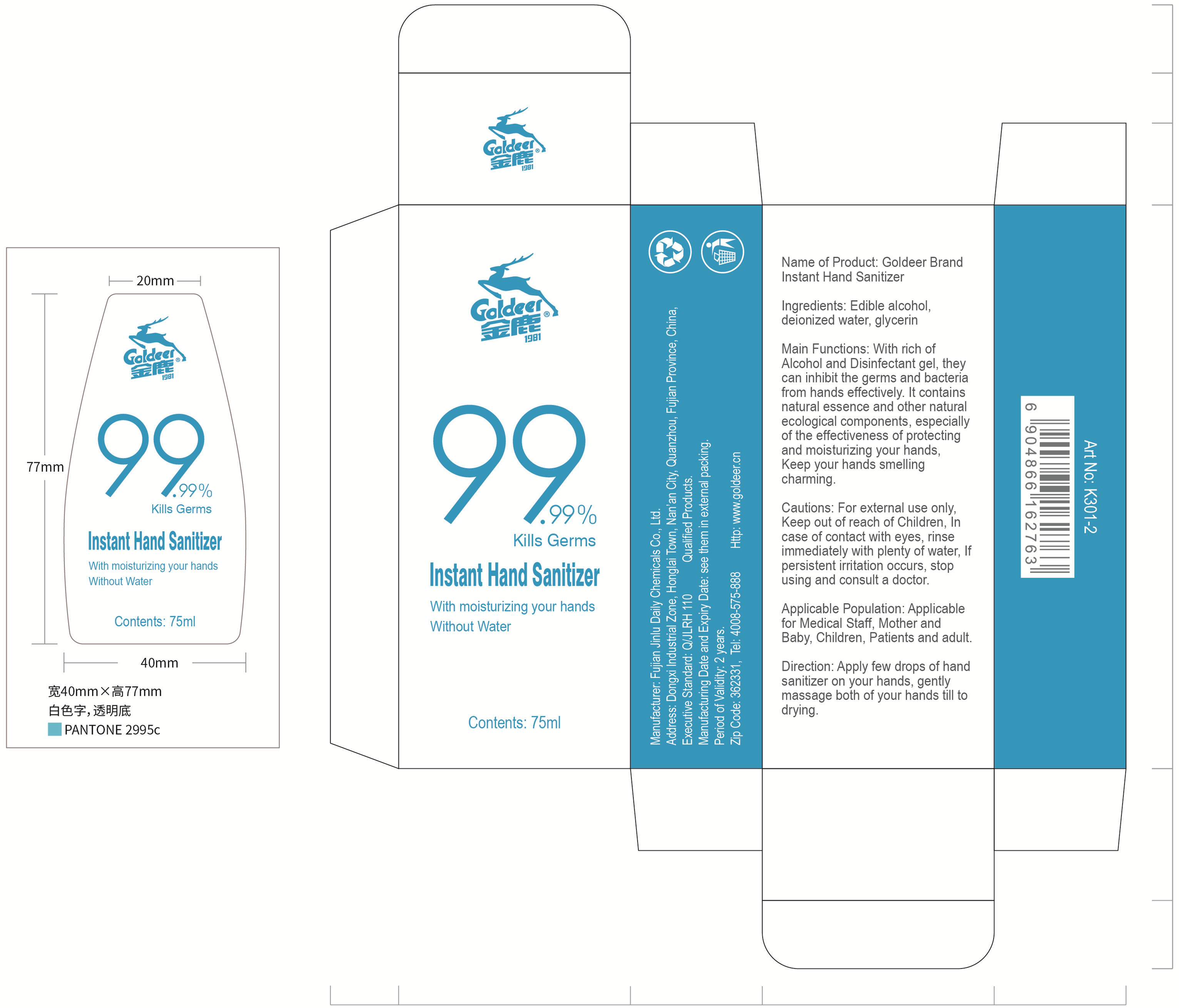 DRUG LABEL: goldeer brand hand sanitizer
NDC: 52976-002 | Form: GEL
Manufacturer: Fujian Jinlu Daily Chemicals Co.,Ltd
Category: otc | Type: HUMAN OTC DRUG LABEL
Date: 20200410

ACTIVE INGREDIENTS: ALCOHOL 52.5 mL/75 mL
INACTIVE INGREDIENTS: GLYCERIN; TROLAMINE

ACTIVE INGREDIENT

ethanol

INACTIVE INGREDIENT

Glycerin

triethanolamine

DOSAGE AND ADMINISTRATION

a little

PURPOSE

99.99%Kills Germs

keep out of children

INDICATIONS AND USAGE

Apply few drops of hand sanitizer on your hands, genty massage both of your hands fil to drying.

WARNINGS

For external use only, Keep out of reach of Children, In case of contact with eyes, rinse immediately with plenty of water, If persistent itation occurs, stop using and consult a doctor.